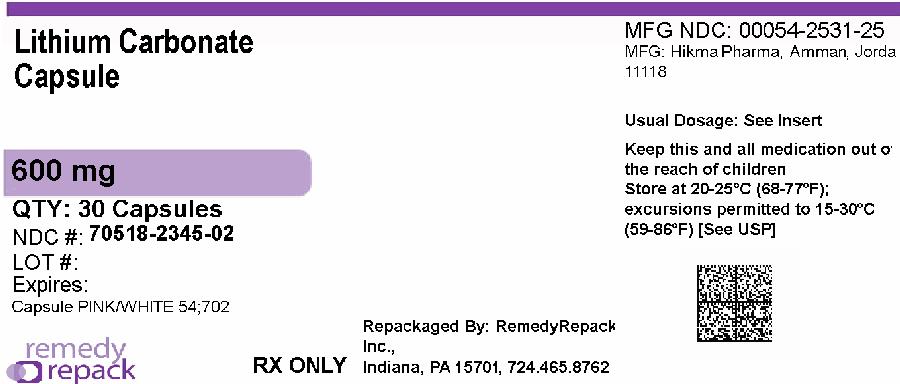 DRUG LABEL: Lithium Carbonate
NDC: 70518-2345 | Form: CAPSULE, GELATIN COATED
Manufacturer: REMEDYREPACK INC.
Category: prescription | Type: HUMAN PRESCRIPTION DRUG LABEL
Date: 20260204

ACTIVE INGREDIENTS: LITHIUM CARBONATE 600 mg/1 1
INACTIVE INGREDIENTS: FD&C RED NO. 40; TALC; GELATIN, UNSPECIFIED; TITANIUM DIOXIDE; FERROSOFERRIC OXIDE; SHELLAC; AMMONIA; ALCOHOL; ISOPROPYL ALCOHOL; BUTYL ALCOHOL; PROPYLENE GLYCOL

HIGHLIGHTS OF PRESCRIBING INFORMATION

These highlights do not include all the information needed to use LITHIUM and LITHIUM CARBONATE safely and effectively. See full prescribing information for LITHIUM and LITHIUM CARBONATE.
LITHIUM oral solution, for oral use
LITHIUM CARBONATE tablets, for oral use
LITHIUM CARBONATE capsules, for oral use
Initial U.S. Approval: 1970

WARNING: LITHIUM TOXICITY

See full prescribing information for complete boxed warning.

Lithium toxicity is closely related to serum lithium concentrations, and can occur at doses close to therapeutic concentrations. Facilities for prompt and accurate serum lithium determinations should be available before initiating therapy (2.3, 5.1).

1 INDICATIONS AND USAGE

Lithium is a mood-stabilizing agent indicated as monotherapy for the treatment of bipolar I disorder:

- Treatment of acute manic and mixed episodes in patients 7 years and older (1)
- Maintenance treatment in patients 7 years and older (1)

2 DOSAGE AND ADMINISTRATION

- Recommended starting dosage for adults and pediatric patients over 30 kg (2.2):
  - Tablets or Capsules: 300 mg, three times daily, or
  - Oral Solution: 8mEq lithium (5 mL) three times daily
- Recommended starting dosage for pediatric patients 20 to 30 kg (2.2):
  - Tablets or Capsules: 300 mg twice daily, or
  - Oral Solution: 8mEq (5mL), twice daily
- Obtain serum lithium concentration assay after 3 days, drawn 12 hours after the last oral dose and regularly until patient is stabilized.
- Acute Manic or Mixed Episodes (patients 7 years and older): Titrate to serum lithium concentrations 0.8 to 1.2 mEq/L (2.2).
- Maintenance Treatment for Bipolar I Disorder (patients 7 years and older): Titrate to serum lithium concentrations 0.8 to 1 mEq/L (2.2).
- Pre-treatment Screening: Evaluate renal function, vital signs, electrolytes, thyroid function, concurrent medications, and pregnancy status (2.1).
- Mild to Moderate Renal Impairment (CLer 30 to 89 mL/min): Start with dosages less than those for patients with normal renal function, titrate slowly with frequent monitoring (2.5).
- Severe Renal Impairment (CLer<30mL/min): Avoid use of lithium (2.5).

3 DOSAGE FORMS AND STRENGTHS

- Capsules: 600 mg of lithium carbonate (3)

4 CONTRAINDICATIONS

Known hypersensitivity to any inactive ingredient in the drug product. (4)

5 WARNINGS AND PRECAUTIONS

- Lithium-Induced Polyuria: May develop during initiation of treatment. Increases risk of lithium toxicity. Educate patient to avoid dehydration. Monitor for lithium toxicity and metabolic acidosis. Discontinue lithium or treat with amiloride as a therapeutic agent (5.2).
- Hyponatremia: Symptoms are more severe with faster-onset hyponatremia. Dehydration from protracted sweating, diarrhea, or elevated temperatures from infection increases risk of hyponatremia and lithium toxicity. Educate patients on maintaining a normal diet with salt and staying hydrated. Monitor for and treat hyponatremia and lithium toxicity, which may necessitate a temporary reduction or cessation of lithium and infusion of serum sodium (5.3).
- Lithium-Induced Chronic Kidney Disease: Associated with structural changes in patients on chronic lithium therapy. Monitor kidney function during treatment with lithium (5.4).
- Encephalopathic Syndrome: Increased risk in patients treated with lithium and an antipsychotic. Monitor routinely for changes to cognitive function (5.5).
- Hypothyroidism and Hyperthyroidism: Monitor thyroid function regularly (5.7).
- Hypercalcemia and Hyperparathyroidism: Associated with long-term lithium use. Monitor serum calcium (5.8).

6 ADVERSE REACTIONS

Common Adverse Reactions:

- Adult Patients: fine hand tremor, polyuria, mild thirst, nausea, general discomfort during initial treatment (6)
- Pediatric Patients (7-17 years): nausea/vomiting, polyuria, thyroid abnormalities, tremor, thirst/polydipsia, dizziness, rash/dermatitis, ataxia/gait disturbance, decreased appetite, and blurry vision (6)

To report SUSPECTED ADVERSE REACTIONS, contact West-Ward Pharmaceuticals Corp. at 1-800-962-8364 or FDA at 1-800-FDA-1088 or www.fda.gov/medwatch.

7 DRUG INTERACTIONS

- Diuretics, NSAID, renin-angiotensin system antagonists, or metronidazole may increase lithium serum concentrations. Recommend frequent monitoring of serum lithium concentration and adjust dosage when necessary. (2.3, 7.1)
- Serotonergic Agents: Increased risk of serotonin syndrome when co-administered with lithium. (5.6, 7.1)
- Antipsychotics: There have been reports of neurologic adverse reactions in patients treated with lithium and an antipsychotic, ranging from extrapyramidal symptoms to neuroleptic malignant syndrome. (5.5, 7.1)

8 USE IN SPECIFIC POPULATIONS

- Pregnancy: May cause fetal and/or neonatal harm (8.1)
- Renal Impairment: Use caution during dose selection, starting with dosages less than those for patients with normal renal function while carefully monitoring for side effects (2.5, 6)

FULL PRESCRIBING INFORMATION

WARNING: LITHIUM TOXICITY

Lithium toxicity is closely related to serum lithium concentrations, and can occur at doses close to therapeutic concentrations. Facilities for prompt and accurate serum lithium determinations should be available before initiating treatment [see Dosage and Administration (2.3), Warnings and Precautions (5.1)] .

1 INDICATIONS AND USAGE

Lithium is a mood-stabilizing agent indicated as monotherapy for the treatment of bipolar I disorder:

- Treatment of acute manic and mixed episodes in patients 7 years and older [see Clinical Studies (14)]
- Maintenance treatment in patients 7 years and older [see Clinical Studies (14)]

2 DOSAGE AND ADMINISTRATION

2.1 Pre-treatment Screening

Before initiating treatment with lithium, renal function, vital signs, serum electrolytes, and thyroid function should be evaluated. Concurrent medications should be assessed, and if the patient is a woman of childbearing potential, pregnancy status and potential should be considered.

2.2 Recommended Dosage

See Table 1 for dosage recommendations for acute and maintenance treatment of bipolar I disorder in adult and pediatric patients (7 to 17 years).

Obtain serum lithium concentration assay after 3 days, drawn 12 hours after the last oral dose and regularly until patient is stabilized. Fine hand tremor, polyuria, and thirst may occur during initial therapy for the acute manic phase and may persist throughout treatment. Nausea and general discomfort may also appear during the first few days of lithium administration. These adverse reactions may subside with continued treatment, concomitant administration with food, or temporary reduction or cessation of dosage.

Table 1. Lithium Dosing for Bipolar I Disorder
Patient Group | Formulation | Starting Dose | 1. Dose Titration | Acute Goal |  | Maintenance Goal
Patient Group | Formulation | Starting Dose | 1. Dose Titration | Serum Level | Usual Dose | Serum Level | Usual Dose
Adult and Pediatric Patients over 30 kg | Tablets or capsules | 300 mg three times daily | 1. 300 mg every 3 days | 0.8 to 1.2 mEq/L | 600 mg two to three times daily | 0.8 to 1.0 mEq/L | 300 to 600 mg two to three times daily
Adult and Pediatric Patients over 30 kg | Liquid | 8 mEq (5 mL) three times daily | 1. 8 mEq (5 mL) every 3 days | 0.8 to 1.2 mEq/L | 16 mEq (10mL) two to three times daily | 0.8 to 1.0 mEq/L | 8 to 16 mEq (5 to 10 mL) two to three times daily
Pediatric Patients 20 to 30 kg | Tablets or capsules | 300 mg twice daily | 1. 300 mg weekly | 0.8 to 1.2 mEq/L | 600 to 1500 mg in divided doses daily | 0.8 to 1.0 mEq/L | 600 to 1200 mg in divided doses daily
Pediatric Patients 20 to 30 kg | Liquid | 8 mEq (5 mL) twice daily | 1. 8 mEq (5 mL) weekly | 0.8 to 1.2 mEq/L | 16 to 40 mEq (10 to 25 mL) in divided doses daily | 0.8 to 1.0 mEq/L | 16 to 32 mEq (10 to 20 mL) in divided doses daily

Each 5 mL of Lithium Oral Solution contains 8 mEq of lithium ion (Li+) which is equivalent to the amount of lithium in 300 mg of lithium carbonate. See Table 2 for lithium carbonate and lithium oral solution dose conversion.

Table 2. Lithium Carbonate and Lithium Oral Solution Dose Conversion

Lithium Carbonate Tablets or Capsules | Lithium Oral Solution
150 mg | 4 mEq (2.5 mL)
300 mg | 8 mEq (5 mL)
600 mg | 16 mEq (10 mL)

2.3 Serum Lithium Monitoring

Blood samples for serum lithium determination should be drawn immediately prior to the next dose when lithium concentrations are relatively stable (i.e., 12 hours after the previous dose). Total reliance must not be placed on serum concentrations alone. Accurate patient evaluation requires both clinical and laboratory analysis.

In addition to regular monitoring of serum lithium concentrations for patients on maintenance treatment, serum lithium concentrations should be monitored after any change in dosage, concurrent medication (e.g., diuretics, non-steroidal anti-inflammatory drugs, renin-angiotensin system antagonists, or metronidazole), marked increase or decrease in routinely performed strenuous physical activity (such as an exercise program) and in the event of a concomitant disease [see Boxed Warning, Warnings and Precautions (5.1), Drug Interactions (7.1)] .

Patients abnormally sensitive to lithium may exhibit toxic signs at serum concentrations that are within what is considered the therapeutic range. Geriatric patients often respond to reduced dosage, and may exhibit signs of toxicity at serum concentrations ordinarily tolerated by other patients [see Specific Populations (8.5)] .

2.4 Dosage Adjustments during Pregnancy and the Postpartum Period

If the decision is made to continue lithium treatment during pregnancy, monitor serum lithium concentrations and adjust the dosage as needed in a pregnant woman because renal lithium clearance increases during pregnancy. Avoid sodium restriction or diuretic administration. To decrease the risk of postpartum lithium intoxication, decrease or discontinue lithium therapy two to three days before the expected delivery date to reduce neonatal concentrations and reduce the risk of maternal lithium intoxication due to the change in vascular volume which occurs during delivery. At delivery, vascular volume rapidly decreases and the renal clearance of lithium may decrease to pre-pregnancy concentrations. Restart treatment at the preconception dose when the patient is medically stable after delivery with careful monitoring of serum lithium concentrations [see Warnings and Precautions (5.1) and Use in Specific Populations (8.1)] .

2.5 Dosage Adjustments for Patients with Renal Impairment

Start patients with mild to moderately impaired renal function (creatinine clearance 30 to 89 mL/min evaluated by Cockcroft-Gault) with dosages less than those for patients with normal renal function [see Dosage and Administration (2.2)] . Titrate slowly while frequently monitoring serum lithium concentrations and monitoring for signs of lithium toxicity. Lithium is not recommended for use in patients with severe renal impairment (creatinine clearance less than 30 mL/min evaluated by Cockcroft-Gault) [see Use in Specific Populations (8.6)] .

3 DOSAGE FORMS AND STRENGTHS

Each 600 mg capsule for oral administration contains: lithium carbonate USP and is an opaque, light pink-colored cap with white body, imprinted with product identification “54 702” on both the cap and the body and containing a white powder.

4 CONTRAINDICATIONS

Lithium is contraindicated in patients with known hypersensitivity to any inactive ingredient in the lithium carbonate tablet or capsule or lithium citrate products [see Adverse Reactions (6)].

5 WARNINGS AND PRECAUTIONS

5.1 Lithium Toxicity

The toxic concentrations for lithium (≥1.5 mEq/L) are close to the therapeutic range (0.8 to 1.2mEq/L). Some patients abnormally sensitive to lithium may exhibit toxic signs at serum concentrations that are considered within the therapeutic range [see Boxed Warning, Dosage and Administration (2.3)] . Lithium may take up to 24 hours to distribute into brain tissue, so occurrence of acute toxicity symptoms may be delayed.

Neurological signs of lithium toxicity range from mild neurological adverse reactions such as fine tremor, lightheadedness, lack of coordination, and weakness; to moderate manifestations like giddiness, apathy, drowsiness, hyperreflexia, muscle twitching, ataxia, blurred vision, tinnitus, and slurred speech; and severe manifestations such as clonus, confusion, seizure, coma, and death. In rare cases, neurological sequelae may persist despite discontinuing lithium treatment and may be associated with cerebellar atrophy. Cardiac manifestations involve electrocardiographic changes, such as prolonged QT interval, ST and T-wave changes and myocarditis. Renal manifestations include urine concentrating defect, nephrogenic diabetes insipidus, and renal failure. Respiratory manifestations include dyspnea, aspiration pneumonia, and respiratory failure. Gastrointestinal manifestations include nausea, vomiting, diarrhea, and bloating. No specific antidote for lithium poisoning is known [see Overdosage (10)] .

The risk of lithium toxicity is increased by:

- Recent onset of concurrent febrile illness
- Concomitant administration of drugs which increase lithium serum concentrations by pharmacokinetic interactions or drugs affecting kidney function [ see Drug Interactions (7)].
- Acute ingestion
- Impaired renal function
- Volume depletion or dehydration
- Significant cardiovascular disease
- Changes in electrolyte concentrations (especially sodium and potassium)

Monitor for signs and symptoms of lithium toxicity. If symptoms occur, decrease dosage or discontinue lithium treatment.

5.2 Lithium-Induced Polyuria

Chronic lithium treatment may be associated with diminution of renal concentrating ability, occasionally presenting as nephrogenic diabetes insipidus, with polyuria and polydipsia. The concentrating defect and natriuretic effect characteristic of this condition may develop within weeks of lithium initiation. Lithium can also cause renal tubular acidosis, resulting in hyperchloremic metabolic acidosis. Such patients should be carefully managed to avoid dehydration with resulting lithium retention and toxicity. This condition is usually reversible when lithium is discontinued, although for patients treated with long-term lithium, nephrogenic diabetes insipidus may be only partly reversible upon discontinuation of lithium. Amiloride may be considered as a therapeutic agent for lithium-induced nephrogenic diabetes insipidus.

5.3 Hyponatremia

Lithium can cause hyponatremia by decreasing sodium reabsorption by the renal tubules, leading to sodium depletion. Therefore, it is essential for patients receiving lithium treatment to maintain a normal diet, including salt, and an adequate fluid intake (2500 to 3000 mL) at least during the initial stabilization period. Decreased tolerance to lithium has also been reported to ensue from protracted sweating or diarrhea and, if such occur, supplemental fluid and salt should be administered under careful medical supervision and lithium intake reduced or suspended until the condition is resolved. In addition, concomitant infection with elevated temperatures may also necessitate a temporary reduction or cessation of medication.

Symptoms are also more severe with faster-onset hyponatremia. Mild hyponatremia (i.e., serum Na > 120 mEq/L) can be asymptomatic. Below this threshold, clinical signs are usually present, consisting mainly of changes in mental status, such as altered personality, lethargy, and confusion. For more severe hyponatremia (serum Na < 115 mEq/L), stupor, neuromuscular hyperexcitability, hyperreflexia, seizures, coma, and death can result. During treatment of hyponatremia, serum sodium should not be elevated by more than 10 to 12 mEq/L in 24 hours, or 18 mEq/L in 48 hours. In the case of severe hyponatremia where severe neurologic symptoms are present, a faster infusion rate to correct serum sodium concentration may be needed. Patients rapidly treated or with serum sodium <120mEq/L are more at risk of developing osmotic demyelination syndrome (previously called central pontine myelinolysis). Occurrence is more common among patients with alcoholism, undernutrition, or other chronic debilitating illness. Common signs include flaccid paralysis, dysarthria. In severe cases with extended lesions patients may develop a locked-in syndrome (generalized motor paralysis). Damage often is permanent. If neurologic symptoms start to develop during treatment of hyponatremia, serum sodium correction should be suspended to mitigate the development of permanent neurologic damage.

5.4 Lithium-Induced Chronic Kidney Disease

The predominant form of chronic renal disease associated with long-term lithium treatment is a chronic tubulointerstitial nephropathy (CTIN). The biopsy findings in patients with lithium induced CTIN include tubular atrophy, interstitial fibrosis, sclerotic glomeruli, tubular dilation, and nephron atrophy with cyst formation. The relationship between renal function and morphologic changes and their association with lithium treatment has not been established. CTIN patients might present with nephrotic proteinuria (>3.0g/dL), worsening renal insufficiency and/or nephrogenic diabetes insipidus. Postmarketing cases consistent with nephrotic syndrome in patients with or without CTIN have also been reported. The biopsy findings in patients with nephrotic syndrome include minimal change disease and focal segmental glomerulosclerosis. The discontinuation of lithium in patients with nephrotic syndrome has resulted in remission of nephrotic syndrome.

Kidney function should be assessed prior to and during lithium treatment. Routine urinalysis and other tests may be used to evaluate tubular function (e.g., urine specific gravity or osmolality following a period of water deprivation, or 24-hour urine volume) and glomerular function (e.g., serum creatinine, creatinine clearance, or proteinuria). During lithium treatment, progressive or sudden changes in renal function, even within the normal range, indicate the need for re-evaluation of treatment.

5.5 Encephalopathic Syndrome

An encephalopathic syndrome, characterized by weakness, lethargy, fever, tremulousness and confusion, extrapyramidal symptoms, leukocytosis, elevated serum enzymes, BUN and fasting blood glucose, has occurred in patients treated with lithium and an antipsychotic. In some instances, the syndrome was followed by irreversible brain damage. Because of a possible causal relationship between these events and the concomitant administration of lithium and antipsychotics, patients receiving such combined treatment should be monitored closely for early evidence of neurological toxicity and treatment discontinued promptly if such signs appear. This encephalopathic syndrome may be similar to or the same as neuroleptic malignant syndrome (NMS).

5.6 Serotonin Syndrome

Lithium can precipitate serotonin syndrome, a potentially life-threatening condition. The risk is increased with concomitant use of other serotonergic drugs (including selective serotonin reuptake inhibitors, serotonin and norepinephrine reuptake inhibitors, triptans, tricyclic antidepressants, fentanyl, tramadol, tryptophan, buspirone, and St. John’s Wort) and with drugs that impair metabolism of serotonin, i.e., MAOIs [see Drug Interactions (7.1)].

Serotonin syndrome signs and symptoms may include mental status changes (e.g., agitation, hallucinations, delirium, and coma), autonomic instability (e.g., tachycardia, labile blood pressure, dizziness, diaphoresis, flushing, hyperthermia), neuromuscular symptoms (e.g., tremor, rigidity, myoclonus, hyperreflexia, incoordination), seizures, and gastrointestinal symptoms (e.g., nausea, vomiting, diarrhea).

Monitor all patients taking lithium for the emergence of serotonin syndrome. Discontinue treatment with lithium and any concomitant serotonergic agents immediately if the above symptoms occur, and initiate supportive symptomatic treatment. If concomitant use of lithium with other serotonergic drugs is clinically warranted, inform patients of the increased risk for serotonin syndrome and monitor for symptoms.

5.7 Hypothyroidism or Hyperthyroidism

Lithium is concentrated within the thyroid and can inhibit thyroid synthesis and release which can lead to hypothyroidism. Where hypothyroidism exists, careful monitoring of thyroid function during lithium stabilization and maintenance allows for correction of changing thyroid parameters, if any. Where hypothyroidism occurs during lithium stabilization and maintenance, supplemental thyroid treatment may be used. Paradoxically, some cases of hyperthyroidism have been reported including Grave’s disease, toxic multinodular goiter and silent thyroiditis.

Monitor thyroid function before the initiation of treatment, at three months and every six to twelve months while treatment is ongoing. If serum thyroid tests warrant concern, monitoring should occur more frequently.

5.8 Hypercalcemia and Hyperparathyroidism

Long-term lithium treatment is associated with persistent hyperparathyroidism and hypercalcemia. When clinical manifestations of hypercalcemia are present, lithium withdrawal and change to another mood stabilizer may be necessary. Hypercalcemia may not resolve upon discontinuation of lithium, and may require surgical intervention. Lithium-induced cases of hyperparathyroidism are more often multiglandular compared to standard cases. False hypercalcemia due to plasma volume depletion resulting from nephrogenic diabetes insipidus should be excluded in individuals with mildly increased serum calcium. Monitor serum calcium concentrations regularly.

5.9 Unmasking of Brugada Syndrome

There have been postmarketing reports of a possible association between treatment with lithium and the unmasking of Brugada Syndrome. Brugada Syndrome is a disorder characterized by abnormal electrocardiographic (ECG) findings and a risk of sudden death. Lithium should be avoided in patients with Brugada Syndrome or those suspected of having Brugada Syndrome. Consultation with a cardiologist is recommended if: (1) treatment with lithium is under consideration for patients suspected of having Brugada Syndrome or patients who have risk factors for Brugada Syndrome, e.g., unexplained syncope, a family history of Brugada Syndrome, or a family history of sudden unexplained death before the age of 45 years, (2) patients who develop unexplained syncope or palpitations after starting lithium treatment.

5.10 Pseudotumor Cerebri

Cases of pseudotumor cerebri (increased intracranial pressure and papilledema) have been reported with lithium use. If undetected, this condition may result in enlargement of the blind spot, constriction of visual fields and eventual blindness due to optic atrophy. Consider discontinuing lithium if this syndrome occurs.

6 ADVERSE REACTIONS

The following adverse reactions are described in greater detail in other sections:

- Acute Lithium Toxicity [see Warnings and Precautions (5.1)]
- Lithium-Induced Polyuria [see Warnings and Precautions (5.2)]
- Hyponatremia [see Warnings and Precautions (5.3)]
- Lithium-Induced Chronic Kidney Disease [see Warnings and Precautions (5.4)]
- Encephalopathic Syndrome [see Warnings and Precautions (5.5)]
- Serotonin Syndrome [see Warnings and Precautions (5.6)]
- Hypothyroidism or Hyperthyroidism [see Warnings and Precautions (5.7)]
- Hypercalcemia and Hyperparathyroidism [see Warnings and Precautions (5.8)]
- Unmasking of Brugada Syndrome [see Warnings and Precautions (5.9)]
- Pseudotumor Cerebri [see Warnings and Precautions (5.10)]

6.1 Clinical Trials Experience

Because clinical trials are conducted under widely varying conditions, adverse reaction rates observed in clinical trials of a drug cannot be directly compared to rates in the clinical trials of another drug and may not reflect the rates observed in clinical practice.

Pediatric Patients (7 to 17 years):

Bipolar I Disorder: The following findings are based on an 8-week, placebo-controlled study for acute manic or mixed episodes of bipolar I disorder in pediatric patients 7 to 17 years (N= 81). In this study, lithium was administered at daily doses ranging from 300 to 3600 (mean dose 1483 mg ± 584) with serum levels ranging from 0 to 2.0 (mean level 0.98 mEq/L ± 0.47).

Common Adverse Reactions (incidence ≥ 5% and at least twice the rate of placebo): nausea/vomiting, polyuria, thyroid abnormalities, tremor, thirst/polydipsia, dizziness, rash/dermatitis, ataxia/gait disturbance, decreased appetite, and blurry vision.

Adverse Reactions Occurring at an Incidence of 2% or More in Lithium-Treated Pediatric Patients: Adverse reactions associated with the use of lithium (incidence of 2% or greater, rounded to the nearest percent, and lithium incidence greater than placebo) that occurred during acute therapy (up to 8-weeks in pediatric patients with bipolar disorder) are shown in Table 3.

Table 3: Adverse Reactions Reported in 2% or More of Pediatric Patients on Lithium and That Occurred at Greater Incidence Than in the Placebo Group in the 8-Week Acute Bipolar Trial

System Organ Class/ Preferred Term | Placebo N=28; % | Lithium N=53; %
Gastrointestinal Disorders
1. Nausea/vomiting | 29 | 57
General Disorders
1. Fatigue | 4 | 26
Genitourinary Disorders
1. Polyuria (Including Enuresis) | 14 | 38
Investigations
1. Increased TSH | 0 | 25
Metabolism and nutrition disorders
1. Thirst/polydipsia | 11 | 28
1. Decreased appetite | 4 | 9
Nervous system disorders
1. Ataxia/gait disturbance | 0 | 13
1. Blurry vision | 0 | 9
1. Disorientation | 0 | 6
1. Dizziness | 7 | 23
1. Tremor | 7 | 32
Skin and subcutaneous tissue disorders
1. Rash/dermatitis | 0 | 13

Adult Patients:

The following adverse reactions have been identified following use of lithium. Because these reactions are reported voluntarily from a population of uncertain size, it is not always possible to reliably estimate their frequency or establish a causal relationship to drug exposure.

Central Nervous System: tremor, muscle hyperirritability (fasciculations, twitching, clonic movements of whole limbs), hypertonicity, ataxia, choreoathetotic movements, hyperactive deep tendon reflexes, extrapyramidal symptoms including acute dystonia, cogwheel rigidity, blackout spells, epileptiform seizures, slurred speech, dizziness, vertigo, downbeat nystagmus, incontinence of urine or feces, somnolence, psychomotor retardation, restlessness, confusion, stupor, coma, tongue movements, tics, tinnitus, hallucinations, poor memory, slowed intellectual functioning, startled response, worsening of organic brain syndromes, myasthenic syndromes (rarely).

EEG Changes: diffuse slowing, widening of frequency spectrum, potentiation and disorganization of background rhythm.

Cardiovascular: conduction disturbance (mostly sinus node dysfunction with possibly severe sinus bradycardia and sinoatrial block), ventricular tachyarrhythmia, peripheral vasculopathy (resembling Raynaud’s Syndrome).

ECG Changes: reversible flattening, isoelectricity or rarely inversion of T-waves, prolongation of the QTc interval.

Gastrointestinal: anorexia, nausea, vomiting, diarrhea, gastritis, salivary gland swelling, abdominal pain, excessive salivation, flatulence, indigestion.

Genitourinary: glycosuria, decreased creatinine clearance, albuminuria, oliguria, and symptoms of nephrogenic diabetes insipidus including polyuria, thirst, and polydipsia.

Dermatologic: drying and thinning of hair, alopecia, anesthesia of skin, chronic folliculitis, xerosis cutis, psoriasis onset or exacerbation, generalized pruritus with or without rash, cutaneous ulcers, angioedema, drug reaction with eosinophilia and systemic symptoms (DRESS).

Autonomic Nervous System: blurred vision, dry mouth, impotence/sexual dysfunction.

Miscellaneous: fatigue, lethargy, transient scotoma, exopthalmos, dehydration, weight loss, leukocytosis, headache, transient hyperglycemia, hypermagnesemia, excessive weight gain, edematous swelling of ankles or wrists, dysgeusia/taste distortion (e.g., metallic or salty taste), thirst, swollen lips, tightness in chest, swollen and/or painful joints, fever, polyarthralgia, and dental caries.

7 DRUG INTERACTIONS

7.1 Drugs Having Clinically Important Interactions with Lithium

Table 4: Clinically Important Drug Interactions with Lithium

Diuretics
Clinical Impact: | Diuretic-induced sodium loss may reduce lithium clearance and increase serum lithium concentrations .
Intervention: | More frequent monitoring of serum electrolyte and lithium concentrations. Reduce lithium dosage based on serum lithium concentration and clinical response [see Dosage and Administration (2.3), Warning and Precautions (5.3)].
Non-Steroidal Anti-inflammatory Drugs (NSAID)
Clinical Impact: | NSAID decrease renal blood flow, resulting in decreased renal clearance and increased serum lithium concentrations.
Intervention: | More frequent serum lithium concentration monitoring. Reduce lithium dosage based on serum lithium concentration and clinical response [see Dosage and Administration (2.3)] .
Renin-Angiotensin System Antagonists
Clinical Impact: | Concomitant use increase steady-state serum lithium concentrations.
Intervention: | More frequent monitoring of serum lithium concentration. Reduce lithium dosage based on serum lithium concentration and clinical response [see Dosage and Administration (2.3)] .
Serotonergic Drugs
Clinical Impact: | Concomitant use can precipitate serotonin syndrome.
Intervention: | Monitor patients for signs and symptoms of serotonin syndrome, particularly during lithium initiation. If serotonin syndrome occurs, consider discontinuation of lithium and/or concomitant serotonergic drugs [see Warnings and Precautions (5.6)] .
Nitroimidazole Antibiotics
Clinical Impact: | Concomitant use may increase serum lithium concentrations due to reduced renal clearance.
Intervention: | More frequent monitoring of serum lithium concentration. Reduce lithium dosage based on serum lithium concentration and clinical response [see Dosage and Administration (2.3)] .
Acetazolamide, Urea, Xanthine Preparations, Alkalinizing Agents
Clinical Impact: | Concomitant use can lower serum lithium concentrations by increasing urinary lithium excretion.
Intervention: | More frequent serum lithium concentration monitoring. Increase lithium dosage based on serum lithium concentration and clinical response [see Dosage and Administration (2.3)] .
Methyldopa, Phenytoin and Carbamazepine
Clinical Impact: | Concomitant use may increase risk of adverse reactions of these drugs.
Intervention: | Monitor patients closely for adverse reactions of methyldopa, phenytoin, and carbamazepine.
Iodide Preparations
Clinical Impact: | Concomitant use may produce hypothyroidism.
Intervention: | Monitor patients for signs or symptoms of hypothyroidism [see Warnings and Precautions (5.7)] .
Calcium Channel Blocking Agents (CCB)
Clinical Impact: | Concomitant use may increase the risk of neurologic adverse reactions in the form of ataxia, tremors, nausea, vomiting, diarrhea and/or tinnitus.
Intervention: | Monitor for neurologic adverse reactions.
Atypical and Typical Antipsychotic Drugs
Clinical Impact: | Reports of neurotoxic reactions in patients treated with both lithium and an antipsychotic, ranging from extrapyramidal symptoms to neuroleptic malignant syndrome, as well as reports of an encephalopathic syndrome in few patients treated with concomitant therapy [see Warnings and Precautions (5.5)] .
Intervention: | Monitor for neurologic adverse reactions.
Sodium-Glucose Cotransporter 2 (SGLT2) inhibitor
Clinical Impact: | Concomitant use of lithium with an SGLT2 inhibitor may decrease serum lithium concentrations.
Intervention: | Monitor serum lithium concentration more frequently during SGLT2 inhibitor initiation and dosage changes.
Neuromuscular Blocking Agents
Clinical Impact: | Lithium may prolong the effects of neuromuscular blocking agents.
Intervention: | Monitor for prolonged paralysis.

8 USE IN SPECIFIC POPULATIONS

8.1 Pregnancy

Risk Summary:

Lithium may cause harm when administered to a pregnant woman. Early voluntary reports to international birth registries suggested an increase in cardiovascular malformations, especially for Ebstein’s anomaly, with first trimester use of lithium. Subsequent case-control and cohort studies indicate that the increased risk for cardiac malformations is likely to be small; however, the data are insufficient to establish a drug-associated risk. There are concerns for maternal and/or neonatal lithium toxicity during late pregnancy and the postpartum period [see Clinical Considerations]. Published animal developmental and toxicity studies in mice and rats report an increased incidence of fetal mortality, decreased fetal weight, increased fetal skeletal abnormalities, and cleft palate (mouse fetuses only) with oral doses of lithium that produced serum concentrations similar to the human therapeutic range. Other published animal studies report adverse effects on embryonic implantation in rats after lithium administration. Advise pregnant women of the potential risk to a fetus.

The background risk of major birth defects and miscarriage for the indicated population(s) is unknown. In the U.S. general population, the estimated background risk of major birth defects and miscarriage in clinically recognized pregnancies is 2 to 4% and 15 to 20%, respectively.

Clinical Considerations:

Dose Adjustments During Pregnancy and the Postpartum Period: If the decision is made to continue lithium treatment during pregnancy, serum lithium concentrations should be monitored and the dosage adjusted during pregnancy. Two to three days prior to delivery, lithium dosage should be decreased or discontinued to reduce the risk of maternal and/or neonatal toxicity. Lithium may be restarted in the post-partum period at preconception doses in medically stable patients as long as serum lithium levels are closely monitored [see Dosage and Administration (2.4), Warnings and Precautions (5.1)] .

Fetal/Neonatal Adverse Reactions: Lithium toxicity may occur in neonates who were exposed to lithium in late pregnancy. A floppy baby syndrome including neurological, cardiac, and hepatic abnormalities that are similar to those seen with lithium toxicity in adults have been observed. Symptoms include hypotonia, respiratory distress syndrome, cyanosis, lethargy, feeding difficulties, depressed neonatal reflexes, neonatal depression, apnea, and bradycardia. Monitor neonates and provide supportive care until lithium is excreted and toxic signs disappear, which may take up to 14 days.

Consider fetal echocardiography between 16 and 20 weeks gestation in a woman with first trimester lithium exposure because of the potential increased risk of cardiac malformations.

8.2 Lactation

Risk Summary:

Limited published data reports the presence of lithium carbonate in human milk with breast milk levels measured at 0.12 to 0.7 mEq or 40 to 45% of maternal plasma levels. Infants exposed to lithium during breastfeeding may have plasma levels that are 30 to 40% of maternal plasma levels. Signs and symptoms of lithium toxicity such as hypertonia, hypothermia, cyanosis, and ECG changes have been reported in some breastfed neonates and infants. Increased prolactin levels have been measured in lactating women, but the effects on milk production are not known. Breastfeeding is not recommended with maternal lithium use; however, if a woman chooses to breastfeed, the infant should be closely monitored for signs of lithium toxicity. Discontinue breastfeeding if a breastfed infant develops lithium toxicity.

Clinical Considerations:

Consider regular monitoring of lithium levels and thyroid function in a breastfed infant.

8.4 Pediatric Use

The safety and effectiveness of lithium for monotherapy treatment of acute manic or mixed episodes of bipolar I disorder and maintenance monotherapy of bipolar I disorder in pediatric patients ages 7 to 17 years of age have been established in an acute-phase clinical trial of 8 weeks in duration followed by a 28-week randomized withdrawal phase [see Dosage and Administration (2.1), Adverse Reactions (6.1), Clinical Pharmacology (12.3), Clinical Studies (14)] .

The safety and effectiveness of lithium has not been established in pediatric patients less than 7 years of age with bipolar I disorder.

8.5 Geriatric Use

Clinical studies of lithium carbonate tablets did not include sufficient numbers of subjects aged 65 and over to determine whether they respond differently from younger subjects. Other reported clinical experience has not identified differences in response between the elderly and younger patients. In general, dose selection for an elderly patient should be cautious, usually starting at the low end of the dosing range, reflecting the greater frequency of decreased hepatic, renal, or cardiac function, and of concomitant disease or other treatment.

Lithium is known to be substantially excreted by the kidneys, and the risk of toxic reactions to this drug may be greater in patients with impaired renal function. Because elderly patients are more likely to have decreased renal function, care should be taken in dose selection, and it may be useful to monitor renal function.

8.6 Renal Impairment

As lithium is eliminated primarily through the kidney, lithium renal clearance is decreased in patients with abnormal renal function, and the risk of lithium intoxication increases considerably in this setting. Lithium should not be used in severe renal insufficiency (creatinine clearance less than 30 mL/min evaluated by Cockcroft-Gault), especially if the condition requires adherence to a low-sodium diet [see Dosage and Administration (2.5)] .

Start patients with mild to moderately impaired renal function (creatinine clearance 30 to 89 mL/min evaluated by Cockcroft-Gault) with lower doses of lithium and titrate slowly while frequently monitoring serum lithium concentrations and for signs of lithium toxicity [see Dosage and Administration (2.5)].

10 OVERDOSAGE

The toxic concentrations for lithium (≥ 1.5 mEq/L) are close to the therapeutic concentrations [see Warnings and Precautions (5.1)] . At lithium concentrations greater than 3 mEq/L, patients may progress to seizures, coma, and irreversible brain damage.

Treatment:

For current information on the management of poisoning or overdosage, contact the National Poison Control Center at 1-800-222-1222 or www.poison.org.

No specific antidote for lithium poisoning is known. Mild symptoms of lithium toxicity can usually be treated by reduction in dose or cessation of the drug.

In severe cases of lithium poisoning, the goal of treatment is elimination of this ion from the patient. Administration of gastric lavage should be performed, but use of activated charcoal is not recommended as it does not significantly absorb lithium ions. Hemodialysis is the treatment of choice as it is an effective and rapid means of removing lithium in patients with severe toxicity. As an alternative option, urea, mannitol and aminophylline can induce a significant increase in lithium excretion. Appropriate supportive care for the patient should be undertaken. Patients with impaired consciousness should have their airway protected and it is critical to correct any volume depletion or electrolyte imbalance. Patients should be monitored to prevent hypernatremia while receiving normal saline and careful regulation of kidney function is of utmost importance.

Serum lithium concentrations should be closely monitored as there may be a rebound in serum lithium concentrations as a result of delayed diffusion from the body tissues. Likewise, during the late recovery phase, lithium should be re-administered with caution taking into account the possible release of significant lithium stores in body tissues.

11 DESCRIPTION

Each tablet for oral administration contains lithium carbonate USP, 300 mg and the following inactive ingredients: calcium stearate, microcrystalline cellulose, povidone, purified water, sodium lauryl sulfate, and sodium starch glycolate.

Each capsule for oral administration contains lithium carbonate USP, 150 mg, 300 mg or 600 mg and the following inactive ingredient: talc. The capsule shells contain black monogramming ink, FD&C Red No. 40 (300 mg and 600 mg only), gelatin and titanium dioxide. The black monogramming ink contains ammonium hydroxide, ethanol, iron oxide black, isopropyl alcohol, N-butyl alcohol, propylene glycol and shellac glaze.

Each 5 mL of solution for oral administration contains lithium ion (Li+), 8 mEq (equivalent to amount of lithium in 300 mg of lithium carbonate), alcohol 0.3% v/v and the following other inactive ingredients: citric acid, purified water, raspberry blend, sodium benzoate and sorbitol solution.

Lithium Oral Solution is a palatable oral dosage form of lithium ion. It is prepared in solution from lithium hydroxide and citric acid in a ratio approximately di-lithium citrate.

Lithium is an element of the alkali-metal group with atomic number 3, atomic weight 6.94, and an emission line at 671 nm on the flame photometer.

The empirical formula for Lithium Citrate is C6H5Li3O7; molecular weight 209.93. Lithium acts as an antimanic.

Lithium Carbonate USP is a granular, white powder with molecular formula Li2CO3 and molecular weight 73.89.

12 CLINICAL PHARMACOLOGY

12.1 Mechanism of Action

The mechanism of action of lithium as a mood stabilizing agent is unknown.

12.3 Pharmacokinetics

Absorption:

After oral administration, lithium is reported to be completely absorbed in the upper gastrointestinal tract. Peak serum concentrations (Tmax) occur 0.25 to 3 hours after oral administration of immediate release preparations and 2 to 6 hours after sustained-release preparations.

Distribution:

The distribution space of lithium approximates that of total body water, and the plasma protein binding is negligible. After equilibrium, the apparent volume of distribution is 0.7 to 1 L/kg.

Metabolism:

Lithium is not metabolized.

Excretion:

Lithium is primarily excreted in urine, proportionally to its serum concentration. Lithium is filtered by the glomerulus, and 80% is reabsorbed by passive diffusion in the proximal tubule. The elimination half-life of lithium is approximately 18 to 36 hours. Lithium excretion in feces is insignificant.

Specific Populations:

Pediatric Use: A pharmacokinetic study of lithium was performed in 39 subjects with bipolar I disorder. Both apparent clearance and apparent volume of distribution increase as body weight increases. A lower dose in patients < 30 kg is necessary to achieve lithium exposures in pediatric patients similar to those observed in adults treated at recommended doses of lithium [see Dosage and Administration (2.2)] . The estimated plasma clearance was 0.59 L/h, 0.79 L/h and 1.17 L/h for pediatric patients weighing 20 kg, 30 kg and 50 kg, respectively.

13 NONCLINICAL TOXICOLOGY

13.1 Carcinogenesis, Mutagenesis, Impairment of Fertility

Carcinogenesis:

There have been no long-term studies performed in animals to evaluate the carcinogenic potential of lithium.

Mutagenesis:

There have been no adequate studies conducted to evaluate the mutagenic and genotoxic potential of lithium.

Impairment of Fertility:

There have been no adequate studies performed in animals at current standards to evaluate the effect of lithium treatment on fertility. However, published studies in male mice and rats administered repeated daily dosing of lithium carbonate report adverse effects on male reproductive organs, decreased spermatogenesis and decreased testosterone levels.

14 CLINICAL STUDIES

The safety and efficacy of lithium as a treatment for acute manic or mixed episodes of bipolar I disorder in pediatric patients (ages 7 to ≤18 years) was demonstrated in an 8-week, randomized, placebo-controlled, parallel group study (NCT01166425). In this study, 81 patients with a Young Mania Rating Scale (YMRS) score of 20 or more were randomized to receive lithium or placebo in a 2:1 ratio. Patients weighing more than 30 kg started lithium at 300 mg three times daily (900 mg/day) and could increase their dose by 300 mg every 3 days. Patients weighing 20 to 30 kg started lithium at 300 mg twice daily (600 mg/day) and could increase their dose by 300 mg weekly. No patients weighing less than 20 kg were enrolled. Lithium (mean serum level 0.98 ± 0.47 mEq/L) was statistically significantly superior to placebo in decreasing acute mania or mixed states as measured by the YMRS (see Table 5).

In a 28-week randomized withdrawal analysis, 31 pediatric patients stabilized on lithium were assigned to either continue lithium or switch to placebo. The group receiving lithium demonstrated superiority to those receiving placebo in all-cause discontinuation (see Table 5).

Table 5: Primary Efficacy Results

Analysis | Treatment Group | Change From Baseline at Week 8 in YMRS Summary Score
Analysis | Treatment Group | N | Mean Baseline Score (SD) | LS Mean Change from Baseline (SE) | Difference [Difference (drug minus placebo) in least-squares mean change from baseline.] (95% CI)
Acute Efficacy | Lithium: | 53 | 29.5 (5.6) | -12.9 (3.1) | -5.5 (-10.5, -0.5)
Acute Efficacy | Placebo: | 28 | 30.0 (6.0) | -7.3 (3.1) | -5.5 (-10.5, -0.5)
Analysis | Treatment Group [Patients analyzed by received treatment.] | All-cause Discontinuation
Analysis | Treatment Group [Patients analyzed by received treatment.] | N |  | Number of Discontinued Subjects | Hazard Ratio [Lithium to placebo.]; (95% CI)
Randomized Withdrawal | Lithium: | 17 |  | 7 (41.2%) | 0.28 (0.10, 0.78)
Randomized Withdrawal | Placebo: | 14 |  | 11 (78.6%) | 0.28 (0.10, 0.78)
SD: standard deviation; SE: standard error; LS Mean: least-squares mean; CI: confidence interval.

16 HOW SUPPLIED/STORAGE AND HANDLING

Lithium Carbonate Capsules USP

600 mg supplied as gelatin capsules having opaque, light pink-colored caps with white bodies, imprinted with product identification “54 702” on both caps and bodies and containing a white powder.

NDC: 70518-2345-00

NDC: 70518-2345-01

NDC: 70518-2345-02

PACKAGING: 100 in 1 BOX

PACKAGING: 1 in 1 POUCH

PACKAGING: 30 in 1 BLISTER PACK

Storage

Store at 20°C to 25°C (68°F to 77°F); excursions permitted to 15°C to 30°C (59°F to 86°F). [See USP Controlled Room Temperature.] Dispense in a tight, child-resistant container as defined in the USP/NF. PROTECT FROM MOISTURE.

Repackaged and Distributed By:

Remedy Repack, Inc.

625 Kolter Dr. Suite #4 Indiana, PA 1-724-465-8762

17 PATIENT COUNSELING INFORMATION

Advise the patient to read FDA-approved patient labeling (Medication Guide).

Dosage and Administration:

Advise patients that lithium is a mood stabilizer, and should only be taken as directed. Emphasize the importance of compliance with the prescribed treatment and to not adjust the dose of lithium without first consulting their healthcare provider. Inform patients that they will need to have regular blood draws to determine if their dose of lithium is appropriate.

Instruct patients not to double the dose if a dose is missed, due to the complexity of individualized dosing and potential for lithium toxicity [see Dosage and Administration (2), Warnings and Precautions (5.1)] .

Lithium Toxicity:

Inform patients on adverse reactions related to lithium toxicity that require medical attention. Advise patients to discontinue lithium treatment and contact their healthcare provider if clinical signs of lithium toxicity such as diarrhea, vomiting, tremor, lack of muscle coordination, drowsiness, abnormal heart rhythm or muscular weakness occur [see Warnings and Precautions (5.1)] .

Lithium-Induced Polyuria:

Counsel patients on the adverse reactions related to lithium-induced polyuria, when to seek medical attention, and the importance of maintaining normal diet with salt and staying hydrated [see Warnings and Precautions (5.2)] .

Hyponatremia:

Counsel patients on the adverse reactions of hyponatremia, when to seek medical attention, the importance of maintaining a normal diet including adequate salt intake and staying hydrated [see Warnings and Precautions (5.3)] . Salt supplements and additional fluids may be required if excessive losses occur.

Serotonin Syndrome:

Caution patients about the risk of serotonin syndrome, particularly with the concomitant use of lithium with other serotonergic drugs including SSRIs, SNRIs, triptans, tricyclic antidepressants, fentanyl, tramadol, tryptophan, buspirone, St. John’s Wort, and with drugs that impair metabolism of serotonin (in particular, MAOIs, both those intended to treat psychiatric disorders and also others, such as linezolid) [see Warnings and Precautions (5.6) and Drug Interactions (7)] .

Drug Interactions:

Advise patients that many drugs can interact with lithium and to inform their doctor and pharmacist if they are taking any over the counter medication, including herbal medication, or are started on a new prescription [see Drug Interactions (7)] .

Somnolence:

Tell patients that lithium may cause somnolence particularly when initiating treatment and to be cautious about operating vehicles or hazardous machinery, until they are reasonably certain that lithium treatment does not affect them adversely [see Adverse Reactions (6)].

Pregnancy:

Advise pregnant women of the potential risk to a fetus and/or neonate [see Use in Specific Populations (8.1)] .

Lactation:

Advise women that breastfeeding is not recommended during treatment with lithium [see Use in Specific Populations (8.2)] .

Repackaged By / Distributed By: RemedyRepack Inc.

625 Kolter Drive, Indiana, PA 15701

(724) 465-8762

Medication Guide

Lithium (LITH-ee-əm) oral solution

Lithium Carbonate tablets

Lithium Carbonate capsules

What is the most important information I should know about Lithium and Lithium Carbonate?

Lithium and Lithium Carbonate can cause serious side effects, including:

- too much lithium in your blood (lithium toxicity). Lithium toxicity that can cause death may happen even if the lithium level in your blood is close to the right level for you. Your healthcare provider will need to monitor your blood levels of lithium to find the best dose for you. Take your Lithium or Lithium Carbonate exactly as your healthcare provider tells you to take it. Stop taking Lithium and Lithium Carbonate and call your healthcare provider right away if you have any symptoms of lithium toxicity including:

- abnormal heartbeat

- vomiting

- diarrhea

- drowsiness

- weak muscles

- blurred vision

- clumsiness

- ringing in your ears

- muscle twitching

Other symptoms may include:

- lightheadedness

- confusion

- bloating

- mood changes

- slurred speech

- breathing problems

- seizure

- coma

What is Lithium and Lithium Carbonate?

Lithium and Lithium Carbonate are prescription medicines called mood-stabilizing agents used alone (monotherapy) for:

- the acute (short-term) treatment of people 7 years of age and older with manic and mixed episodes that happen with bipolar I disorder.
- maintenance treatment of bipolar I disorder in people 7 years of age and older.

It is not known if Lithium and Lithium Carbonate are safe and effective in children under 7 years of age with bipolar I disorder.

Who should not take Lithium or Lithium Carbonate?

Do not take Lithium or Lithium Carbonate if you are allergic to Lithium or any of the ingredients in Lithium Carbonate or Lithium Citrate. See the end of this Medication Guide for a complete list of ingredients in Lithium and Lithium Carbonate.

What should I tell my healthcare provider before taking Lithium or Lithium Carbonate?

Before taking Lithium or Lithium Carbonate, tell your healthcare provider if you:

- have kidney problems

- have heart problems

- have breathing problems

- have thyroid problems

- are pregnant or plan to become pregnant. Lithium and Lithium Carbonate may harm your
  unborn baby.

- are breastfeeding or plan to breastfeed. Lithium and Lithium Carbonate can pass into your breastmilk and may harm your baby. You should not breastfeed during treatment with Lithium or Lithium Carbonate. Talk to your healthcare provider about the best way to feed your baby if you take Lithium or Lithium Carbonate.

Tell your healthcare provider about all the medicines you take, including prescription, over-the-counter medicines, vitamins, and herbal supplements.

Using Lithium and Lithium Carbonate with certain other medicines may affect each other causing possible side effects. Lithium and Lithium Carbonate may affect the way other medicines work, and other medicines may affect how Lithium and Lithium Carbonate works.

Especially tell your healthcare provider if you take:

- MAOIs

- selective serotonin reuptake inhibitors (SSRIs)

- serotonin norepinephrine reuptake inhibitors (SNRIs)

- medicines used to treat migraine headaches called triptans

- tricyclic antidepressants

- fentanyl

- antipsychotic medicines

- tramadol

- tryptophan

- buspirone

- St. John’s Wort

Your healthcare provider can tell you if it is safe to take Lithium or Lithium Carbonate with your other medicines. Do not start or stop any medicines while taking Lithium or Lithium Carbonate without talking to your healthcare provider first.

Know the medicines you take. Keep a list of your medicines to show your healthcare provider and pharmacist when you get a new medicine.

How should I take Lithium and Lithium Carbonate?

- Take your Lithium and Lithium Carbonate exactly as prescribed by your healthcare provider.

- Your healthcare provider will do certain blood tests before starting and during treatment with Lithium and Lithium Carbonate.

- Your healthcare provider may change your dose if needed. Do not change your dose on your own.

- Do not double your dose if a dose is missed. Talk with your healthcare provider if you miss a dose.

- Do not stop taking Lithium or Lithium Carbonate suddenly without talking to your healthcare provider.

- Your healthcare provider may change your Lithium or Lithium Carbonate dose to make sure you are taking the dose that is right for you.

- If you take too much Lithium or Lithium Carbonate, call your healthcare provider or poison control center, or go to the nearest hospital emergency room right away. In case of poisoning, call your poison control center at 1-800-222-1222.

What should I avoid while taking Lithium or Lithium Carbonate?

- Do not drive, operate heavy machinery, or do other dangerous activities when you start taking Lithium or Lithium Carbonate, when your dose is changed, or until you know how Lithium or Lithium Carbonate affects you. Lithium or Lithium Carbonate can make you sleepy. Talk to your healthcare provider about these activities.

- Avoid becoming overheated or dehydrated during exercise and in hot weather. Follow your healthcare provider instructions about the type and amount of liquids you should drink. In some cases, drinking too much liquid can be as unsafe as not drinking enough.

- Do not change the amount of salt in your diet. Changing the amount of salt in your diet could change the amount of Lithium or Lithium Carbonate in your blood.

What are the possible side effects of Lithium and Lithium Carbonate?

See “What is the most important information I should know about Lithium and Lithium Carbonate?”

Lithium and Lithium Carbonate may cause serious side effects, including:

- kidney problems. People who take Lithium or Lithium Carbonate may have to urinate often (polyuria) and have other kidney problems that may affect how their kidneys work. These problems can happen within a few weeks of starting to take Lithium or Lithium Carbonate or after taking Lithium or Lithium Carbonate for a long time.

- low levels of sodium (salt) in your blood (hyponatremia). Lithium and Lithium Carbonate can cause you to lose sodium. Talk to your healthcare provider about your diet and how much fluid you are drinking when starting Lithium or Lithium Carbonate. If you have been sweating more than usual or have had diarrhea, you may need extra salt and more fluids. Talk to your healthcare provider if this happens.

- neurological problems. People who take Lithium or Lithium Carbonate with certain other medicines called antipsychotics may have symptoms such as weakness, tiredness, fever, tremors, and confusion. Talk to your healthcare provider if this happens. Ask if you are not sure about the medicines you take.

- serotonin syndrome. A potentially life-threatening problem called serotonin syndrome can happen when you take Lithium or Lithium Carbonate while you take certain medicines called serotonergic and MAOIs. Symptoms of serotonin syndrome include:

- agitation

- seeing things that are not there

- confusion

- coma

- rapid pulse

- high or low blood pressure

- dizziness

- sweating

- flushing

- fever

- tremors

- stiff muscles

- muscle twitching

- become unstable

- seizures

- nausea

- vomiting

- diarrhea

- thyroid problems.

- high calcium levels in your blood (hypercalcemia) and changes in your parathyroid gland (hyperparathyroidism) that may not go away when you stop taking Lithium or Lithium Carbonate.

- heart problems. People who take Lithium or Lithium Carbonate may find out they also have a heart problem called Brugada Syndrome. People who have unexplained fainting or who have a family history of sudden unexplained death before 45 years of age may have Brugada Syndrome and not know it. If you faint or feel abnormal heartbeats, talk to your healthcare provider right away.

- increased pressure in the brain and swelling in the eye (pseudotumor cerebri) that can cause vision problems or blindness. If you have severe headaches behind your eyes, ringing in the ears, blurred vision, double vision, or brief periods of blindness, talk to your health care provider right away.

The most common side effects of Lithium and Lithium Carbonate, include:

- Adults with manic or mixed episodes of bipolar I disorder:

- hand trembling

- excessive urination

- increased thirst

- nausea

- general discomfort when you start treatment

- Children 7 to 17 years of age with manic or mixed episodes of bipolar I disorder:

- excessive urination

- thyroid problems

- hand trembling

- excessive thirst

- dizziness

- rash

- difficulty walking

- decreased appetite

- blurred vision

- nausea

- vomiting

These are not all the possible side effects of Lithium and Lithium Carbonate.

Call your doctor for medical advice about side effects. You may report side effects to FDA at 1-800-FDA-1088.

How should I store Lithium and Lithium Carbonate?

Store Lithium and Lithium Carbonate at room temperature, between 68°F to 77°F (20°C to 25°C).

Keep capsules and tablets dry and keep in a tightly closed container.

Keep Lithium, Lithium Carbonate, and all medicines out of the reach of children.

General information about the safe and effective use of Lithium and Lithium Carbonate.

Medicines are sometimes prescribed for purposes other than those listed in a Medication Guide. Do not use Lithium or Lithium Carbonate for a condition for which it was not prescribed. Do not give Lithium or Lithium Carbonate to other people, even if they have the same symptoms you have. It may harm them. You can ask your pharmacist or healthcare provider for information about Lithium or Lithium Carbonate that is written for healthcare professionals.

For more information about Lithium and Lithium Carbonate, please call West-Ward Pharmaceuticals Corp. at 1-800-962-8364.

What are the ingredients in Lithium and Lithium Carbonate?

Active ingredient: lithium carbonate, USP (tablets and capsules) and lithium citrate (oral solution).

Inactive ingredients:

Tablets: calcium stearate, microcrystalline cellulose, povidone, purified water, sodium lauryl sulfate, and sodium starch glycolate.

Capsules: talc. The capsule shells contain black monogramming ink, FD&C Red No. 40 (300 mg and 600 mg only), gelatin and titanium dioxide. The black monogramming ink contains ammonium hydroxide, ethanol, iron oxide black, isopropyl alcohol, N-butyl alcohol, propylene glycol and shellac glaze.

Oral solution: alcohol 0.3%, citric acid, purified water, raspberry blend, sodium benzoate and sorbitol solution.

This Medication Guide has been approved by the U.S. Food and Drug Administration.

Revised 10 2020

10008909/10

Repackaged By / Distributed By: RemedyRepack Inc.

625 Kolter Drive, Indiana, PA 15701

(724) 465-8762

PACKAGE LABEL

DRUG: Lithium Carbonate

GENERIC: Lithium Carbonate

DOSAGE: CAPSULE, GELATIN COATED

ADMINSTRATION: ORAL

NDC: 70518-2345-0

NDC: 70518-2345-1

NDC: 70518-2345-2

COLOR: white

SHAPE: CAPSULE

SCORE: No score

SIZE: 18 mm

IMPRINT: 54;702

PACKAGING: 1 in 1 POUCH

OUTER PACKAGING: 100 in 1 BOX

PACKAGING: 30 in 1 BLISTER PACK

ACTIVE INGREDIENT(S):

- LITHIUM CARBONATE 600mg in 1

INACTIVE INGREDIENT(S):

- TALC
- FD&C RED NO. 40
- GELATIN, UNSPECIFIED
- TITANIUM DIOXIDE
- FERROSOFERRIC OXIDE
- SHELLAC
- AMMONIA
- ALCOHOL
- ISOPROPYL ALCOHOL
- BUTYL ALCOHOL
- PROPYLENE GLYCOL